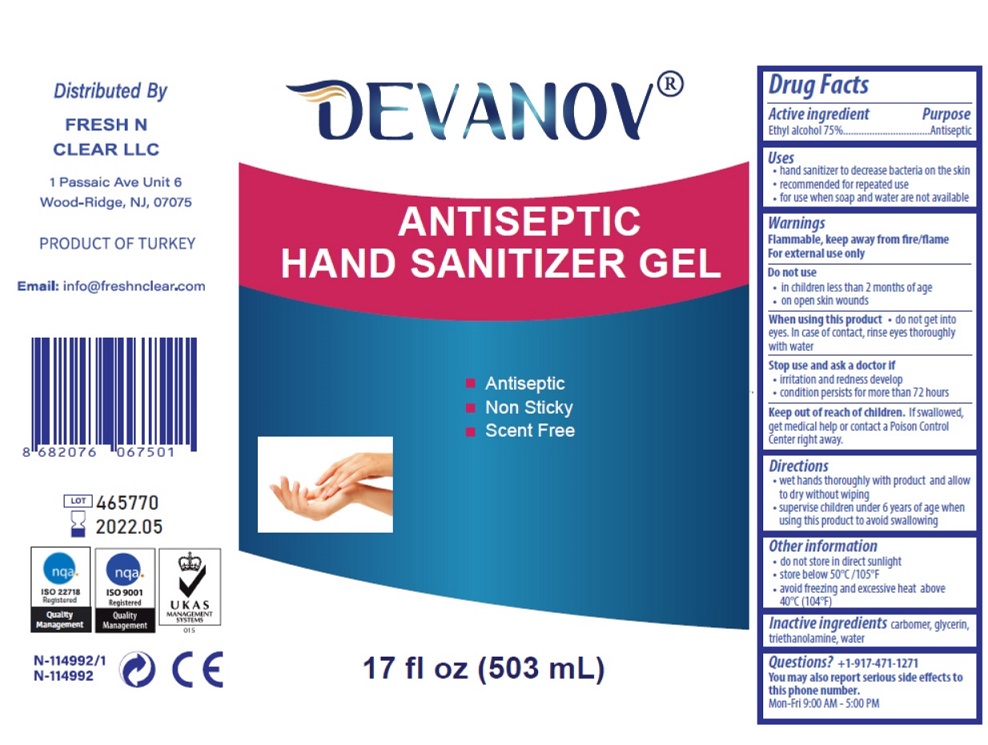 DRUG LABEL: Instant Hand Sanitizer Gel
NDC: 77550-101 | Form: GEL
Manufacturer: MAQAS GROUP GAYRIMENKUL TURIZM SANAYI VE TICARET LIMITED SIRKETI
Category: otc | Type: HUMAN OTC DRUG LABEL
Date: 20200519

ACTIVE INGREDIENTS: ALCOHOL 750 mg/1 mL
INACTIVE INGREDIENTS: CARBOMER HOMOPOLYMER, UNSPECIFIED TYPE; GLYCERIN; TROLAMINE; WATER

DEVANOV® ANTISEPTIC HAND SANITIZER GEL

Active ingredient

Ethyl alcohol 75%

Purpose

Antiseptic

Uses

- hand sanitizer to decrease bacteria on the skin
- recommended for repeated use
- for use when soap and water are not available

Warnings

Flammable, keep away from fire/flame
For external use only

Do not use

- in children less than 2 months of age
- on open skin wounds

When using this product • do not get into eyes. In case of contact, rinse eyes thoroughly with water

Stop use and ask a doctor if

- irritation and redness develop
- condition persists for more than 72 hours

Keep out of reach of children. If swallowed, get medical help or contact a Poison Control Center right away.

Directions

- wet hands thoroughly with product and allow to dry without wiping
- supervise children under 6 years of age when using this product to avoid swallowing

Other information

- do not store in direct sunlight
- store below 50°C /105°F
- avoid freezing and excessive heat above 40°C (104°F)

Inactive ingredients carbomer, glycerin, triethanolamine, water

Questions? +1-917-471-1271
You may also report serious side effects to this phone number.
Mon-Fri 9:00 AM - 5:00 PM

■ Antiseptic

■ Non Sticky

■ Scent Free

Distributed By

FRESH N CLEAR LLC

1 Passaic Ave Unit 6

Wood-Ridge, NJ, 07075

PRODUCT OF TURKEY

Email: info@freshnclear.com

nqa ISO 22718 Registered Quality Management

nqa ISO 9001 Registered Quality Management

U K A S MANAGEMENT SYSTEMS

N-114992/1 CE

N-114992